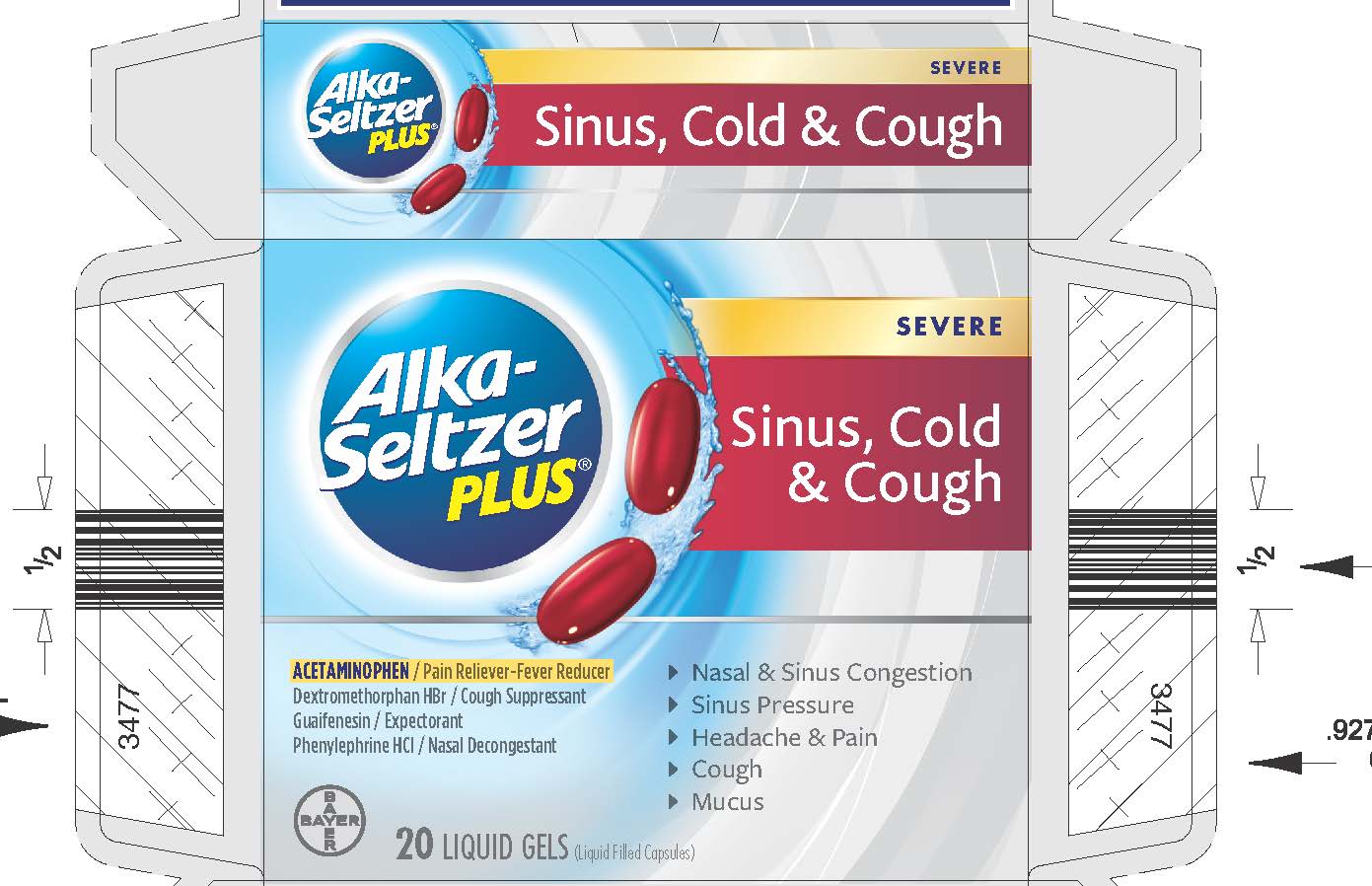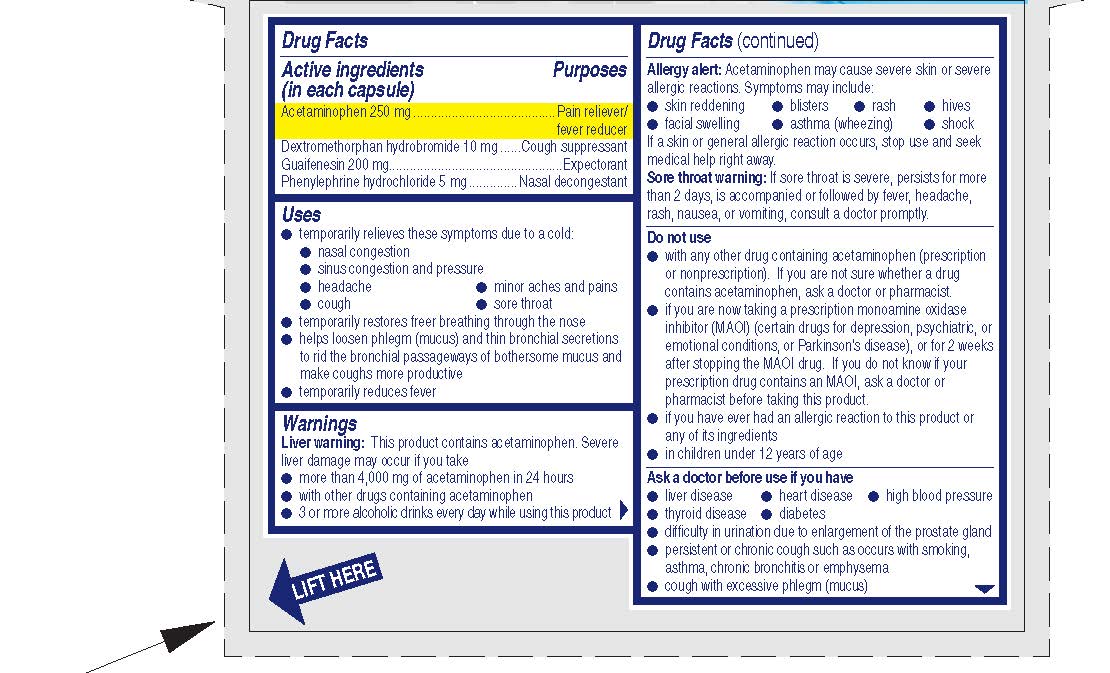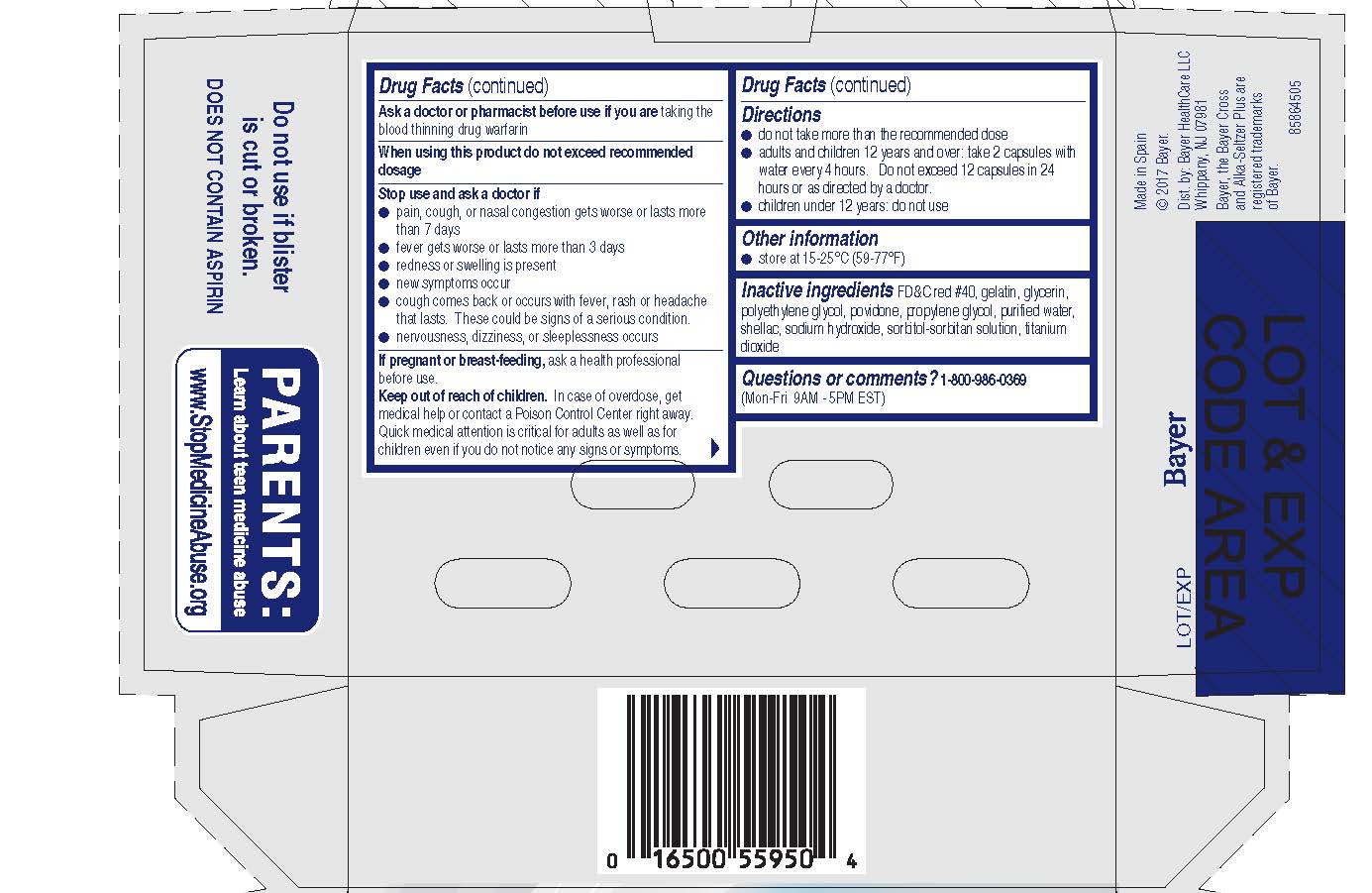 DRUG LABEL: Alka-Seltzer Plus Severe Sinus Cold and Cough
NDC: 0280-0507 | Form: CAPSULE, LIQUID FILLED
Manufacturer: Bayer HealthCare LLC.
Category: otc | Type: HUMAN OTC DRUG LABEL
Date: 20251204

ACTIVE INGREDIENTS: ACETAMINOPHEN 250 mg/1 1; DEXTROMETHORPHAN HYDROBROMIDE 10 mg/1 1; GUAIFENESIN 200 mg/1 1; PHENYLEPHRINE HYDROCHLORIDE 5 mg/1 1
INACTIVE INGREDIENTS: PROPYLENE GLYCOL; WATER; SHELLAC; SODIUM HYDROXIDE; TITANIUM DIOXIDE; FD&C RED NO. 40; GELATIN; GLYCERIN; POLYETHYLENE GLYCOL, UNSPECIFIED; POVIDONE

ALKA SELTZER PLUS SEVERE SINUS COLD & COUGH

Active ingredients (in each capsule) | Purposes
Acetaminophen 250 mg | Pain reliever/fever reducer
Dextromethorphan hydrobromide 10 mg | Cough suppressant
Guaifenesin 200 mg | Expectorant
Phenylephrine hydrochloride 5 mg | Nasal decongestant

Uses

- temporarily relieves these symptoms due to a cold:

· nasal congestion

· sinus congestion and pressure

· headache

· minor aches and pains

· cough

· sore throat

- temporarily restores freer breathing through the nose
- helps loosen phlegm (mucus) and thin bronchial secretions to rid the bronchial passageways of bothersome mucus and make coughs more productive
- temporarily reduces fever

Warnings

Liver warning: This product contains acetaminophen. Severe liver damage may occur if you take

- more than 12 capsules in 24 hours, which is the maximum daily amount for this product
- with other drugs containing acetaminophen
- 3 or more alcoholic drinks every day while using this product

Allergy Alert: acetaminophen may cause severe skin or severe allergic reactions. Symptoms may include:

- skin reddening
- blisters
- rash
- hives
- facial swelling
- asthma (wheezing)
- shock

If a skin or general allergic reaction occurs, stop use and seek medical help right away.

Sore throat warning: If sore throat is severe, persists for more than 2 days, is accompanied or followed by fever, headache, rash, nausea, or vomiting, consult a doctor promptly.

Do Not Use

- with any other drug containing acetaminophen (prescription or nonprescription). If you are not sure whether a drug contains acetaminophen, ask a doctor or pharmacist.
- if you are now taking a prescription monoamine oxidase inhibitor (MAOI) (certain drugs for depression, psychiatric, or emotional conditions, or Parkinson's disease), or for 2 weeks after stopping the MAOI drug. If you do not know if your prescription drug contains an MAOI, ask a doctor or pharmacist before taking this product.
- if you have ever had an allergic reaction to this product or any of its ingredients
- in children under 12 years of age

Ask a doctor before use if you have

- liver disease
- heart disease
- high blood pressure
- thyroid disease
- diabetes
- difficulty in urination due to enlargement of the prostate gland
- persistent or chronic cough such as occurs with smoking, asthma, chronic bronchitis or emphysema
- cough with excessive phlegm (mucus)

Ask a doctor or pharmacist before use if you are taking the blood thinning drug warfarin

When using this product do not exceed recommended dosage

Stop use and ask a doctor if

- pain, cough, or nasal congestion gets worse or lasts more than 7 days
- fever gets worse or lasts more than 3 days
- redness or swelling is present
- new symptoms occur
- cough comes back or occurs with fever, rash or headache that lasts. These could be signs of a serious condition.
- nervousness, dizziness, or sleeplessness occurs

PREGNANCY OR BREAST FEEDING

If pregnant or breast-feeding, ask a health professional before use.

Keep out of reach of children. In case of overdose, get medical help or contact a Poison Control Center right away. Quick medical attention is critical for adults as well as for children even if you do not notice any signs or symptoms.

Directions

- do not take more than the recommended dose
- adults and children 12 years and over: take 2 capsules with water every 4 hours. Do not exceed 12 capsules in 24 hours or as directed by a doctor.
- children under 12 years: do not use

Other information

- store at 15-25ºC (59-77ºF)

INACTIVE INGREDIENT

FD&C red #40, gelatin, glycerin, polyethylene glycol, povidone, propylene glycol, purified water, shellac, sodium hydroxide, sorbitol-sorbitan solution, titanium dioxide

Questions or comments? 1-800-986-0369 (Mon-Fri 9AM - 5PM EST)